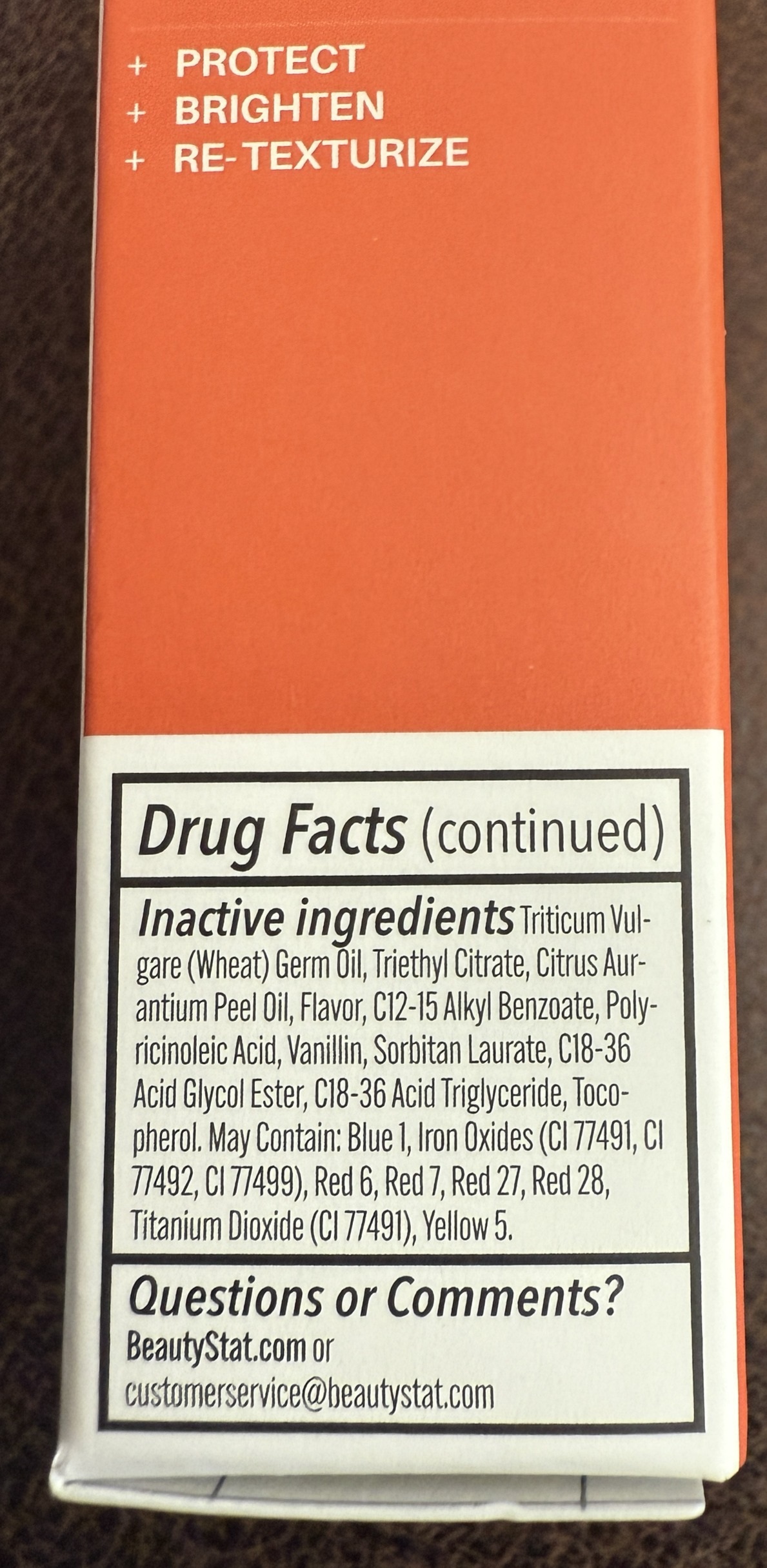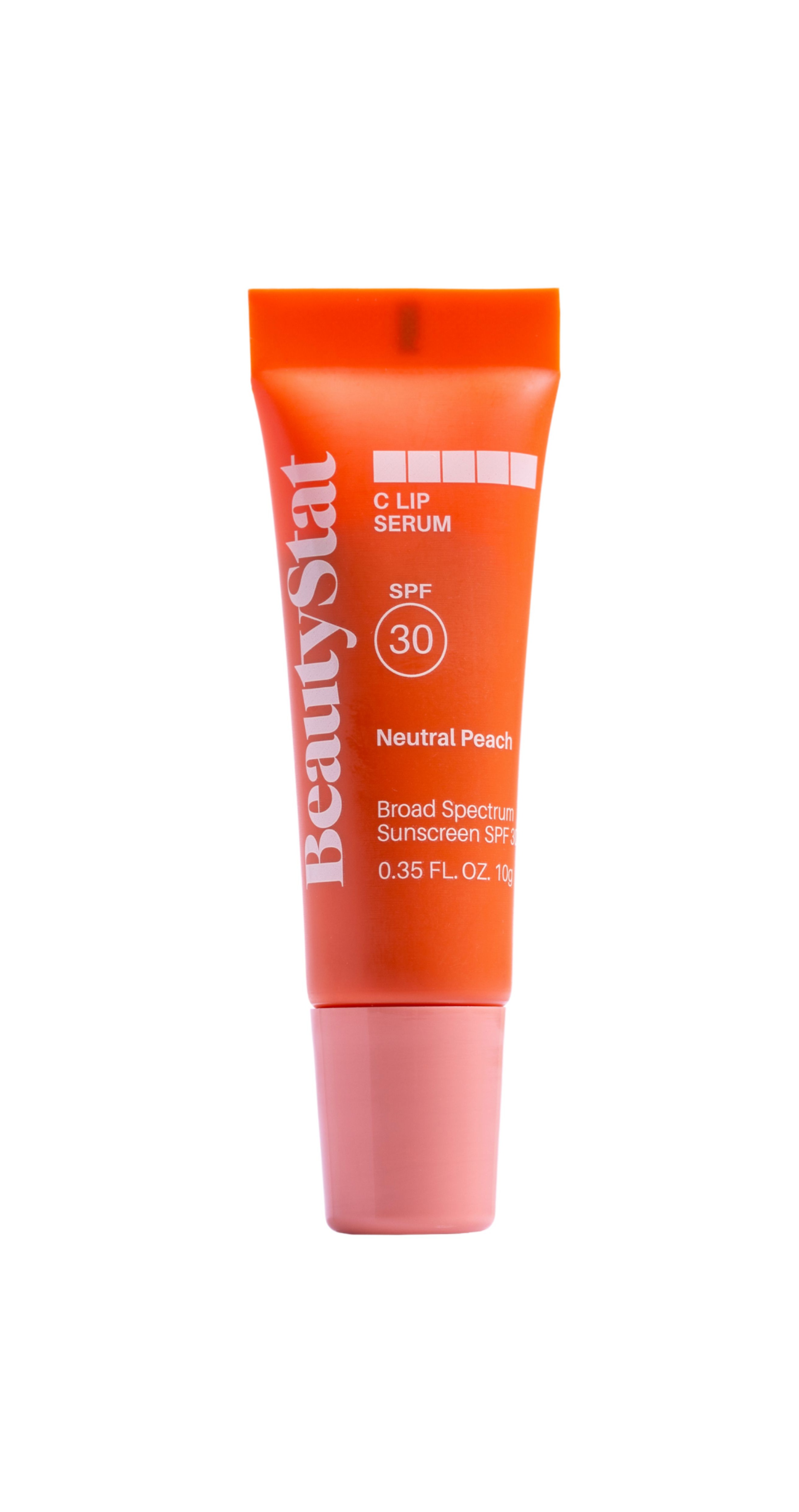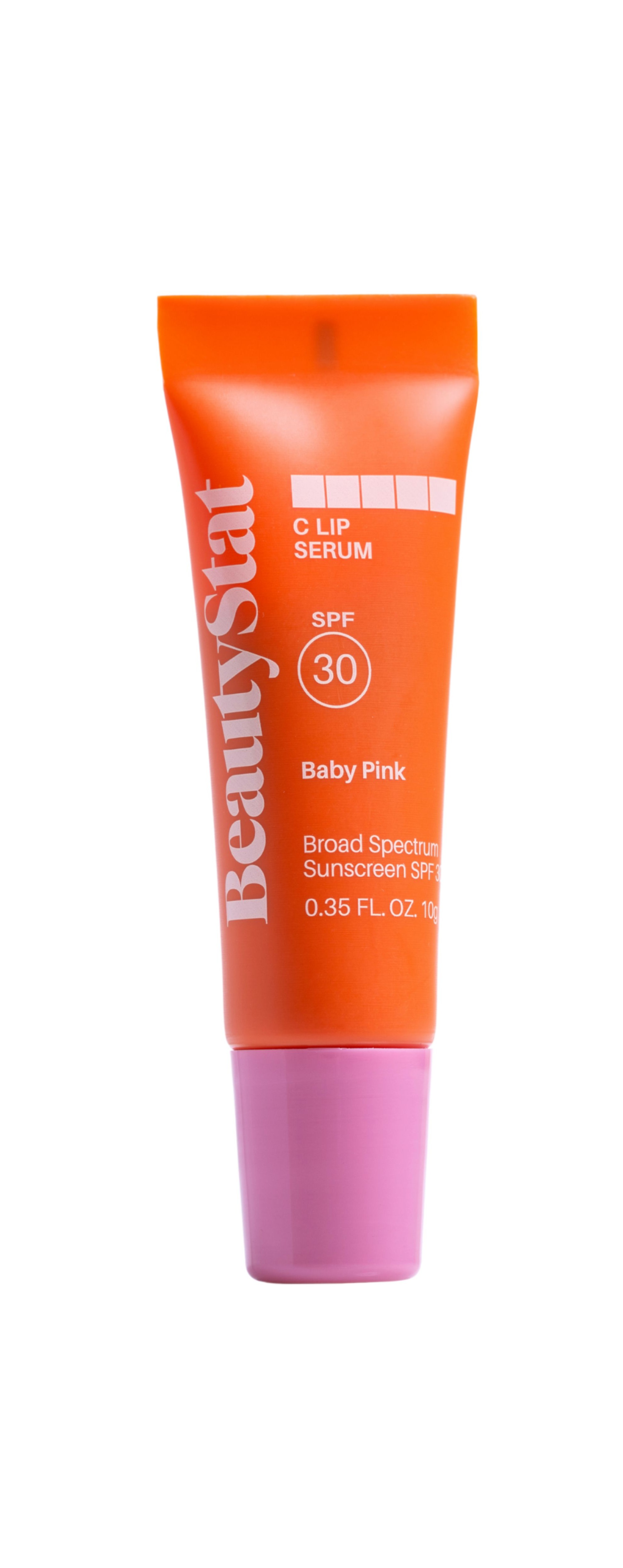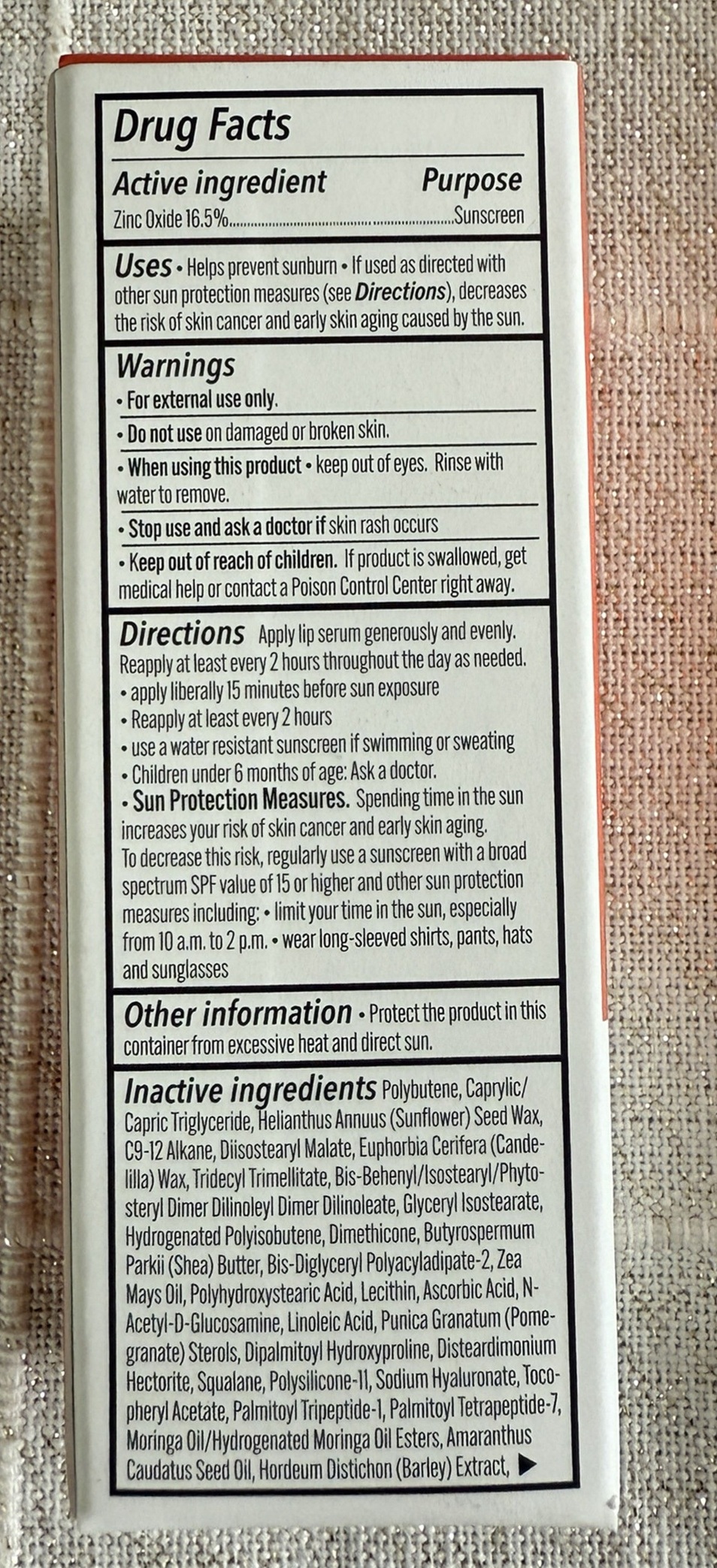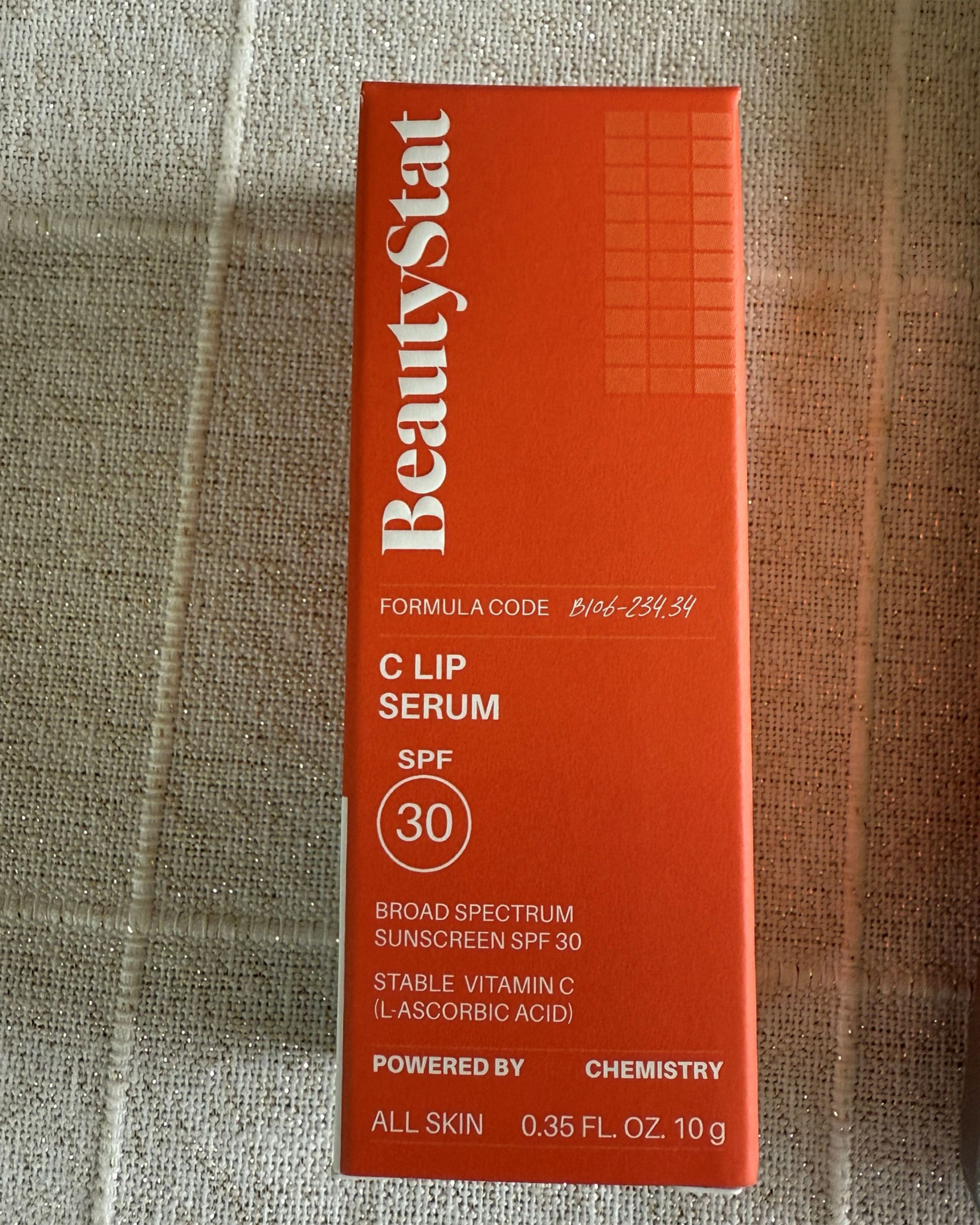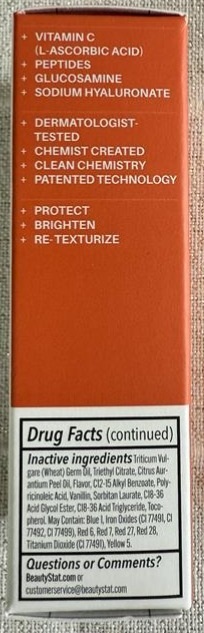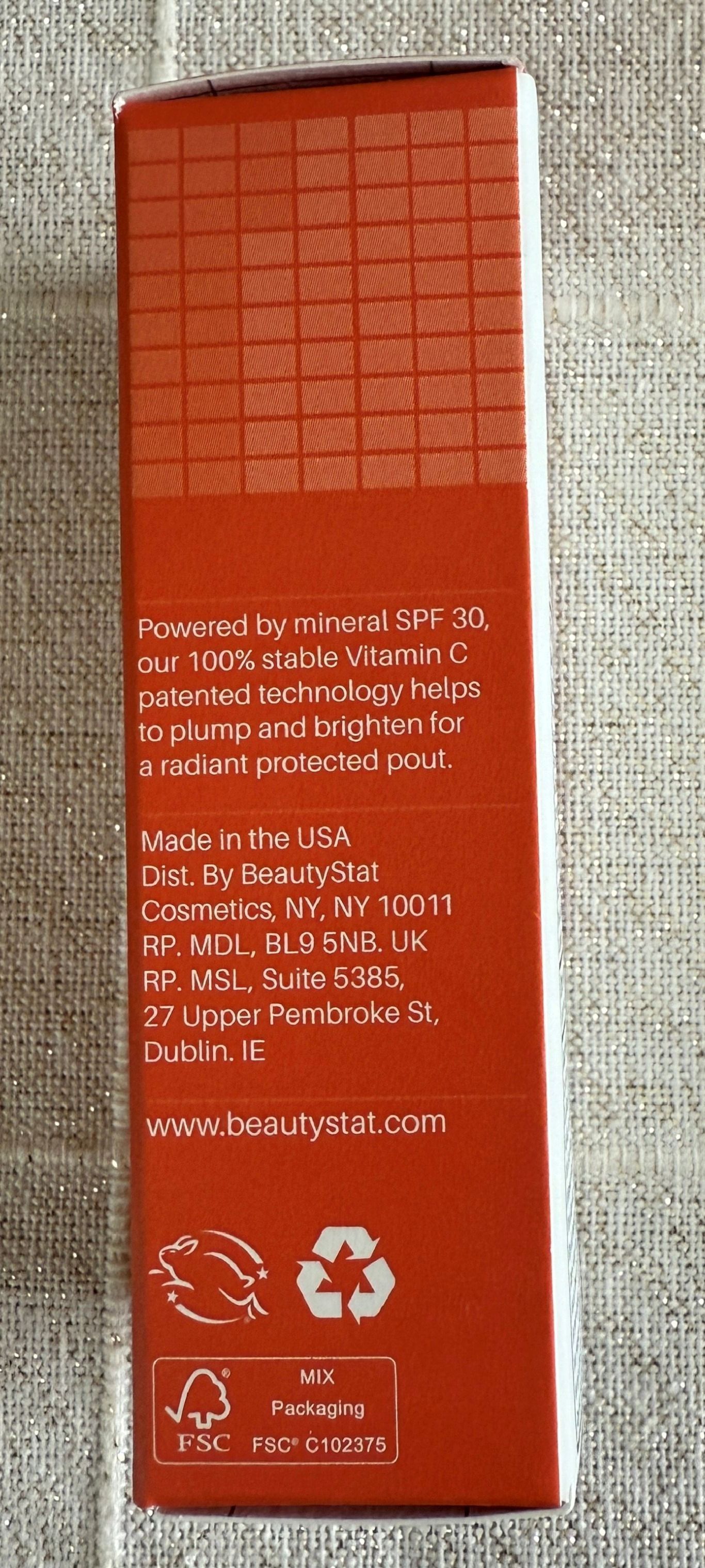 DRUG LABEL: C Lip Serum Mineral Broad Spectrum SPF 30
NDC: 83302-165 | Form: GEL
Manufacturer: Simply Active Cosmetics
Category: otc | Type: HUMAN OTC DRUG LABEL
Date: 20251110

ACTIVE INGREDIENTS: ZINC OXIDE 16.5 g/100 g
INACTIVE INGREDIENTS: C9-12 ALKANE; C12-15 ALKYL BENZOATE; TRIETHYL CITRATE; POLYBUTENE (1400 MW); DISTEARDIMONIUM HECTORITE; BIS-BEHENYL/ISOSTEARYL/PHYTOSTERYL DIMER DILINOLEYL DIMER DILINOLEATE; .ALPHA.-TOCOPHEROL ACETATE; LECITHIN, SOYBEAN; CI 77491; AMARANTHUS CAUDATUS SEED; PALMITOYL TRIPEPTIDE-1; PALMITOYL TETRAPEPTIDE-7; TRIDECYL TRIMELLITATE; DIPALMITOYL HYDROXYPROLINE; LINOLEIC ACID; PIGMENT BLUE 1; PIGMENT RED 7; YELLOW 5; TRITICUM VULGARE (WHEAT) GERM OIL; DIISOSTEARYL MALATE; CI 77492; ASCORBIC ACID; CAPRYLIC/CAPRIC TRIGLYCERIDE; HYDROGENATED POLYISOBUTENE (450 MW); SORBITAN LAURATE; POLYHYDROXYSTEARIC ACID (2300 MW); ZEA MAYS (CORN) OIL; MORINGA OLEIFERA SEED; CITRUS AURANTIUM PEEL OIL; POLYGLYCEROL POLYRICINOLEIC ACID; HELIANTHUS ANNUUS SEED WAX; BUTYROSPERMUM PARKII (SHEA) BUTTER; BIS-DIGLYCERYL POLYACYLADIPATE-2; C18-36 ACID TRIGLYCERIDE; SODIUM HYALURONATE; PUNICA GRANATUM STEROLS; CI 77499; RED 27; RED 28; RED 6; CI 77891; DIMETHICONE/VINYL DIMETHICONE CROSSPOLYMER (SOFT PARTICLE); EUPHORBIA CERIFERA (CANDELILLA) WAX; GLYCERYL ISOSTEARATE; SQUALANE; DIMETHICONE; N-ACETYL-.ALPHA.-D-GLUCOSAMINE; VANILLIN; TOCOPHEROL; HORDEUM VULGARE TOP

ACTIVE INGREDIENT

Zinc Oxide 16.5% … Sunscreen

PURPOSE

Sunscreen

WARNINGS

For external use only

Do not use on damaged or broken skin

When using this product keep out of eyes. Rinse with water to remove.

Stop use and ask a doctor if rash occurs

Keep out of reach of children. If swallowed, get medical help or contact a Poison Control Center right away.

INSTRUCTIONS FOR USE

Apply lip serum generously and evenly
Reapply at least every 2 hours throughout the day as needed
• apply liberally 15 minutes before sun exposure
• reapply at least every 2 hours
• use a water resistant sunscreen if swimming or sweating
• children under 6 months of age: Ask a doctor

Sun Protection Measures: Spending time in the sun increases your risk of skin cancer and early skin aging. To decrease this risk, regularly use a sunscreen with a broad spectrum SPF value of 15 or higher and other sun protection measures including:
• limit your time in the sun, especially from 10 a.m. to 2 p.m.
• wear long-sleeved shirts, pants, hats, and sunglasses

INACTIVE INGREDIENT

Water, Butyloctyl Salicylate, Caprylic/Capric Triglyceride, Polyglyceryl-3 Polyricinoleate, C12-15 Alkyl Benzoate, Glycerin, Sorbitan Sesquioleate, Hydrogenated Poly(C6-14 Olefin), Mica, Glyceryl Dibehenate, Flavor, Microcrystalline Cellulose, Tribehenin, Polyglyceryl-3 Diisostearate, Microcrystalline Wax, Cellulose Gum, Synthetic Fluorphlogopite, Glyceryl Behenate, Lecithin, Caprylyl Glycol, Sodium Chloride, Citric Acid, Ethylhexylglycerin, Polyglyceryl-4 Oleate, Sodium Citrate, Pentaerythrityl Tetra-di-t-butyl Hydroxyhydrocinnamate, Polyhydroxystearic Acid, Triethoxycaprylylsilane, Limonene, Titanium Dioxide (CI 77891), Red 7 Lake (CI 15850)

INDICATIONS AND USAGE

Helps prevent sunburn

If used as directed with other sun protection measures (see Directions), decreases the risk of skin cancer and early skin aging caused by the sun.

DOSAGE AND ADMINISTRATION

Apply lip serum generously and evenly

Apply liberally 15 minutes before sun exposure

Reapply:
- After 40 minutes of swimming or sweating
- Immediately after towel drying
- At least every 2 hours

Use a water resistant sunscreen if swimming or sweating

Children under 6 months of age: Ask a doctor

Keep out of reach of children. If product is swallowed, get medical help or contact a Poison Control Center right away.

PACKAGE LABEL

0.35 FL. OZ. 10g NDC: 83302-165-11

PACKAGE LABEL

0.35 FL. OZ. 10g NDC: 83302-165-11

Outer Carton Drug Facts

PACKAGE LABEL

0.35 FL. OZ. 10 g NDC: 83302-165-11

Outer Carton Front Panel

PACKAGE LABEL

0.35 FL. OZ. 10g NDC: 83302-165-11

Outer Carton Side Panel 1

PACKAGE LABEL

0.35 FL. OZ. 10g NDC: 83302-165-11

Outer Carton Side Panel 2

PACKAGE LABEL

0.35 FL. OZ. 10g NDC: 83302-165-11

Outer Carton Drug Facts Cont Side Panel 1

PACKAGE LABEL

0.35 FL. OZ. 10g NDC: 83302-165-10

Pink Primary

PACKAGE LABEL

0.35 FL. OZ. 10g NDC: 83302-165-10

Pink- Outer Carton Drug Facts Cont

PACKAGE LABEL

0.35 FL. OZ. 10g NDC: 83302-165-10

Pink Outer Drug Facts Panel

PACKAGE LABEL

0.35 FL. OZ. 10g NDC: 83302-165-10

Pink Outer Front Panel

PACKAGE LABEL

0.35 FL. OZ. 10g NDC: 83302-165-10

Outer Pink Side Panel 1

PACKAGE LABEL

0.35 FL. OZ. 10g NDC: 83302-165-10

Pink Outer Side Panel 2